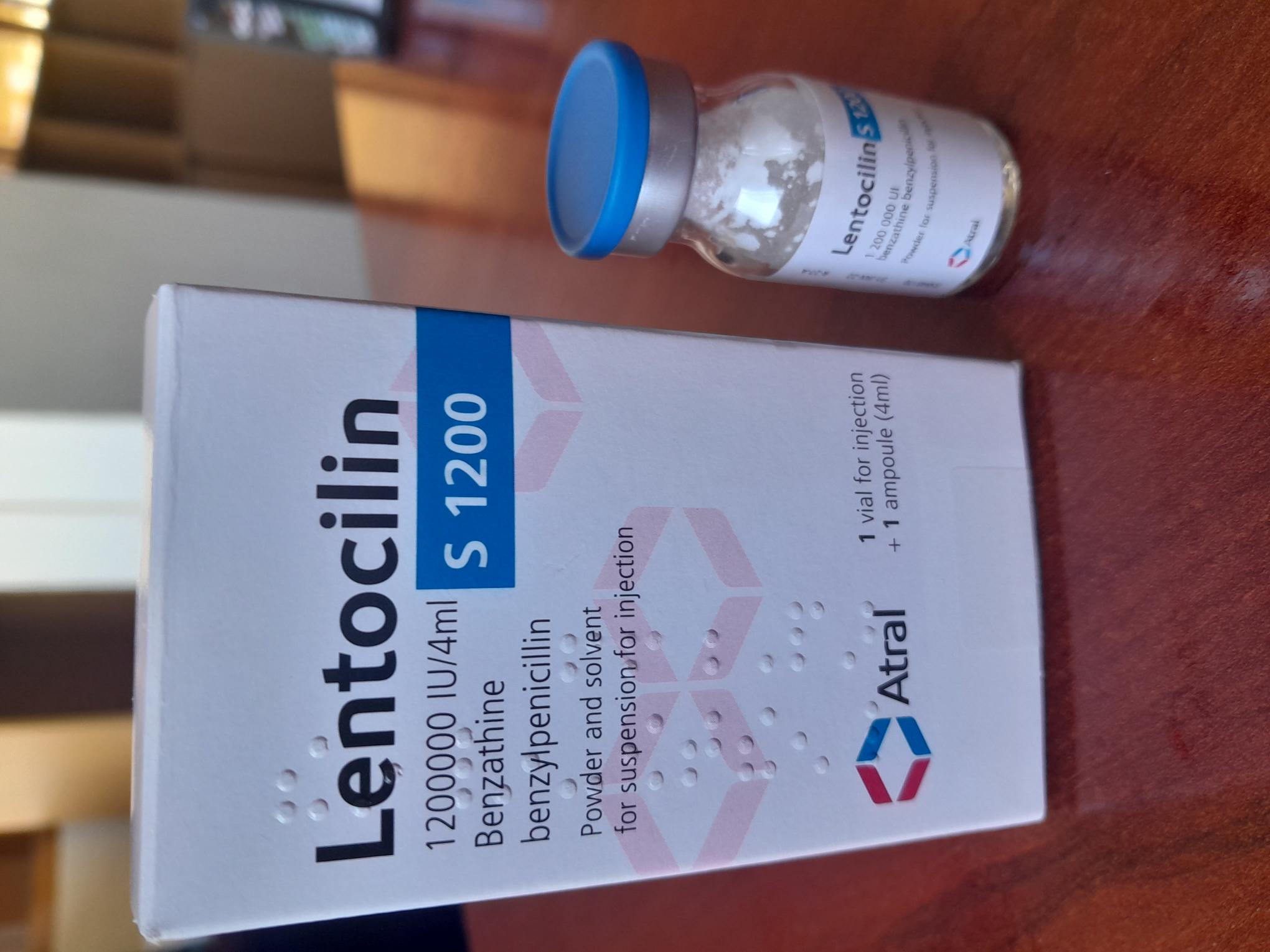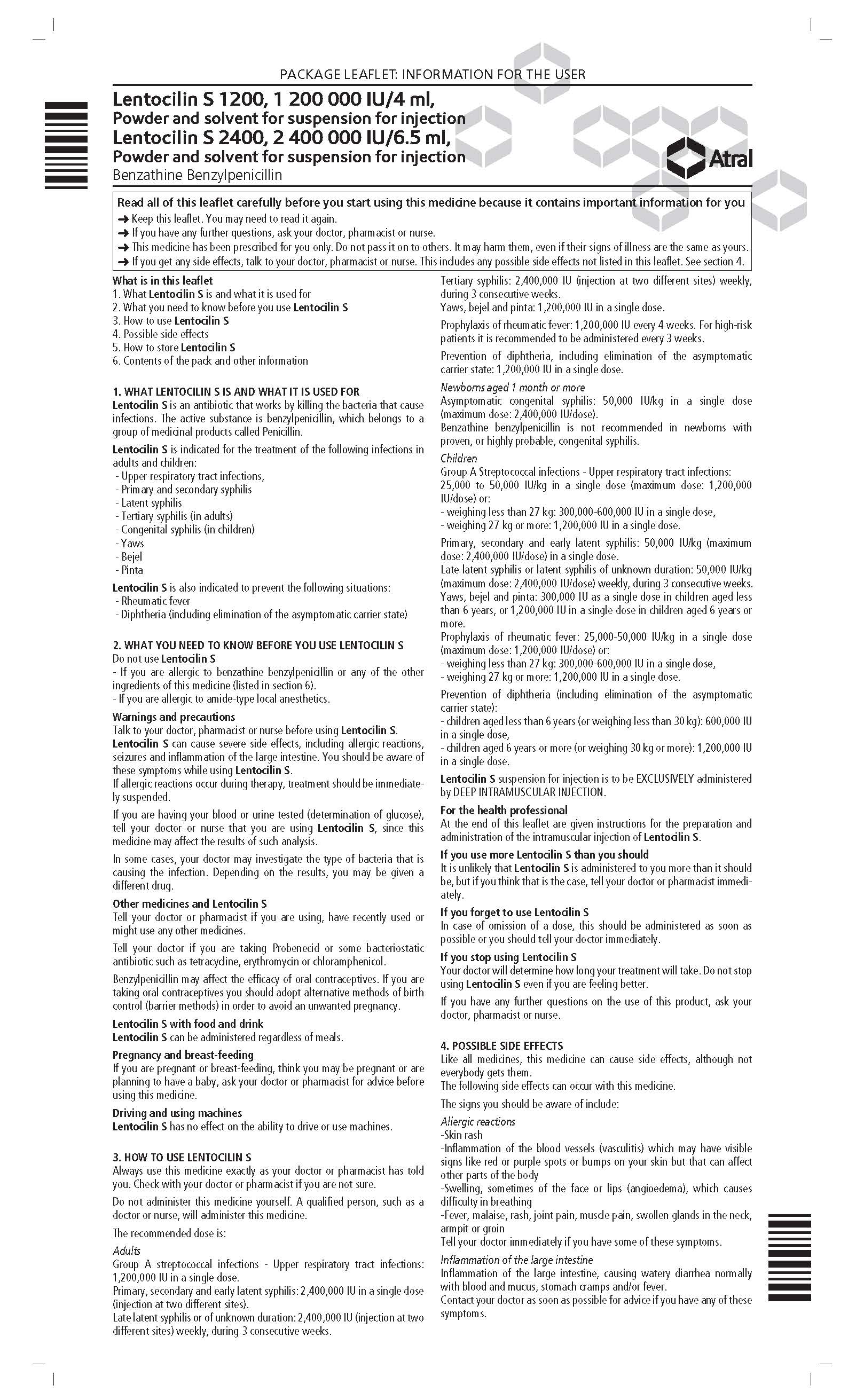 DRUG LABEL: Lentocilin
NDC: 84383-110 | Form: INJECTION, POWDER, FOR SUSPENSION
Manufacturer: LABORATÓRIOS ATRAL, S.A.
Category: prescription | Type: HUMAN PRESCRIPTION DRUG LABEL
Date: 20240607

ACTIVE INGREDIENTS: PENICILLIN G BENZATHINE 1200000 U/4 mL
INACTIVE INGREDIENTS: SOYBEAN LECITHIN 4 mL/4 mL; POLYSORBATE 80 0.2 1/4 mL; WATER 4 mL/4 mL; LIDOCAINE HYDROCHLORIDE 60 mg/4 mL; MONOSODIUM CITRATE 37 mg/4 mL

INDICATIONS AND USAGE

Lentocilin S is indicated for the treatment of the following infections in adults and children:
- Upper respiratory tract infections, namely group A streptococcal infections
- Primary and secondary syphilis
- Latent syphilis
- Tertiary syphilis (in adults)
- Congenital syphilis (in children)
- Yaws
- Bejel
- Pinta

Lentocilin S is also indicated prophylactically in the following situations:
- Rheumatic fever
- Diphtheria (including elimination of the asymptomatic carrier state)

Consideration should be given to official guidelines for appropriate use of antimicrobial agents.

DOSAGE AND ADMINISTRATION

Lentocilin S suspension for injection is to be EXCLUSIVELY administered by DEEP INTRAMUSCULAR (IM) INJECTION. Deep IM administration of this medicine requires a rigorous technique and should be performed only by experienced health technicians and in places prepared for the emergency treatment of a possible anaphylactic reaction.

Posology
Adults
Group A streptococcal infections - Upper respiratory tract infections:
1,200,000 IUunits in a single dose.
Primary, secondary and early latent syphilis: 2,400,000 unitsIU in a single dose (injection at two different sites).
Late latent syphilis or of unknown duration: 2,400,000 unitsIU (injection at two different sites) weekly for 3 consecutive weeks.
Tertiary syphilis: 2,400,000 unitsIU (injection at two different sites) weekly for 3 consecutive weeks.
Yaws, bejel and pinta: 1,200,000 unitsIU in a single dose.

Prophylaxis of rheumatic fever: 1,200,000 unitsIU every 4 weeks. In high-risk patients it is recommended administration of 3 inevery 3 weeks.

Prevention of diphtheria, including elimination of the asymptomatic carrier state: 1,200,000 unitsIU in a single dose.

Newborns aged ≥ 1 month
Asymptomatic congenital syphilis: 50,000 unitsIU/kg in a single dose (maximum dose: 2,400,000 unitsIU/dose).
Benzathine benzylpenicillin is not recommended in newborns with proven or highly probable congenital syphilis.

Children
Group A Streptococcal infections - Upper respiratory tract infections:
25,000 - 50,000 unitsIU/kg in a single dose (maximum dose: 1,200,000 IUunits/dose) or
weight < 27 kg: 300,000-600,000 IU units in a single dose
weight ≥ 27 kg: 1,200,000 unitsIU in a single dose.

- Primary, secondary and early latent syphilis: 50,000 unitsIU/kg (maximum dose: 2,400,000 unitsIU/dose) in a single dose.
- Late latent syphilis or latent syphilis of unknown duration: 50,000 unitsIU/kg (maximum dose: 2,400,000 unitsIU/dose) weekly for 3 weeks.

- Yaws, bejel and pinta: 300,000 unitsIU as a single dose in children aged less than 6 years or 1,200,000 IUunits in a single dose in children aged 6 years and older.

-Prophylaxis of rheumatic fever: 25,000 - 50,000 unitsIU/kg in a single dose (maximum dose: 1,200,000 unitsIU/dose) or
weight < 27 kg: 300,000 - 600,000 unitsIU in a single dose
weight ≥ 27 kg: 1,200,000 unitsIU in a single dose.

Prevention of diphtheria (including elimination of the asymptomatic carrier state):
- children aged < 6 years (or weight < 30 kg): 600,000 unitsIU in a single dose
- children aged ≥ 6 years (or weight ≥ 30 kg): 1,200,000 unitsIU in a single dose.

Special populations

Elderly - Dose adjustment is not necessary. However, since the elderly have a higher likelihood of decreased renal function, this must be taken into consideration during the selection of the posology and may be useful to monitor renal function.

Renal insufficiency - Toxic concentrations of benzylpenicillin following administration of the usually recommended dose are not expected.

Liver insufficiency - Dose adjustment is not necessary.

DOSAGE FORMS AND STRENGTHS

Powder and diluent for suspension for injection: 1200000 units

CONTRAINDICATIONS

Hypersensitivity to the active substance, to other penicillin or to any of the excipients.
Hypersensitivity to lidocaine or local anesthetics of the amide type.

WARNINGS AND PRECAUTIONS

Lentocilin S suspension for injection should ONLY be administered by INTRAMUSCULAR ROUTE. To avoid injury, Lentocilin S suspension should not be administered by intravenous, intraarterial or subcutaneous route, in the adipose layer, into or near a peripheral nerve or blood vessel.
Before injecting the suspension, the position of the needle should be controlled by aspiration. If blood shows up in the syringe, pull back the needle and inject on another site.
Administer Lentocilin S suspension EXCLUSIVELY by DEEP INTRAMUSCULAR INJECTION in the external upper quadrant of the buttock. In children and infants, the IM injections should be done, preferably, in the middle of the external lateral side of the thigh. In infants younger than 2 years, and if considered necessary, the dosage may be divided and administered in two separate sites. The IM injection site should be changed in case of repeated doses.
Deep IM administration of this medicine requires a rigorous technique and should be performed only by experienced health technicians and in places prepared for the emergency treatment of a possible anaphylactic reaction.
A needle to use in the administration of the injectable suspensions should have a minimum internal diameter of 0.8 mm (caliber: 18 gauge).
The deep IM injection should be made slowly and with a constant flow rate to prevent needle blockage. If the needle is clogged, replace it with a new needle.
The deep IM injection should be discontinued if there are signs or symptoms of immediate acute pain, especially in children and infants.
Serious hypersensitivity reactions (anaphylactic reactions), sometimes fatal, have been reported in patients on penicillin therapy. These reactions are more likely to occur in individuals with a history of penicillin hypersensitivity and in atopic individuals. If an allergic reaction occurs, therapy with Lentocillin S should be discontinued immediately and the appropriate therapy instituted.
In case of severe anaphylactic reaction, immediate emergency treatment (including adrenaline, corticosteroids, airway management, oxygen) is required.
Usually, subcutaneous, or intravenous adrenaline is the treatment of choice for an immediate or accelerated hypersensitivity reaction to a penicillin.
Before initiating therapy with benzylpenicillin, careful inquiry should be made concerning previous hypersensitivity reactions to penicillin, cephalosporins, and other beta-lactam antibiotics.
Contact with the penicillin during handling the product should be avoided due to the possibility of skin sensitization.
To minimize the overgrowth of resistant bacteria and maintain the effectiveness of benzylpenicillin, this medicine should only be used in the treatment of infections proven to be caused by susceptible bacteria. Therapy should be based on bacteriological studies (including sensitivity tests) and the patient's clinical response.
Prolonged administration of Lentocilin S can occasionally result in overgrowth of non-susceptible organisms particularly Candida, Pseudomonas or Enterobacter.
Antibiotic treatment modifies the commensal flora of the colon, allowing the growth of Clostridium difficile. This microorganism produces toxins, which are responsible for diarrhea associated to antibiotherapy, which can range from mild diarrhea to fatal colitis. Patients with diarrhea during or even up to two months after treatment with antibiotics should be subject to investigation and differential diagnosis. Confirming pseudomembranous colitis, treatment should be discontinued and, if necessary, use supportive hydro-electrolyte measures, recommended antibiotherapy and protein supplement.
Because of the risk of neurotoxicity, caution is recommended especially in the case of administration of high doses of benzylpenicillin to renal impaired patients.
During prolonged treatment with high doses of benzylpenicillin is recommended to monitor the renal and haematological functions. The use of benzylpenicillin for more than 2 weeks may be associated with an increased risk of neutropenia and incidence of immune complex self-limited sickness-like reactions. Special precautions should be taken in order to avoid intravenous and intraarterial administration or injection into or near major peripheral nerve or blood vessel, since such injections may produce severe and/or permanent neuromuscular damage. In case of evidence of impaired blood flow at the injection site - proximal or distal – an appropriate specialized physician should be immediately consulted.
Special caution is recommended when treating patients with spirochetal infections, particularly syphilis, due to the possibility of a Jarisch - Herxheimer reaction. This is a very common reaction when benzylpenicillin is used to treat syphilis, occurring in 50% of patients with primary syphilis, 75% of those treated for secondary syphilis and 30% of those treated for neurosyphilis. This reaction usually occurs 2-12 hours after initiation of penicillin therapy and is characterized by the occurrence of headache, fever, chills, sweating, sore throat, myalgia, arthralgia, malaise, increased heart rate and an increase in blood pressure followed by its decrease.
This reaction is probably caused by the release of endotoxins from the treponemes and should not be confused with a hypersensitivity reaction. The reaction may be dangerous in cardiovascular syphilis or when there is a serious risk of increased local lesions such as optic atrophy.
It is recommended the use of oxidative enzymatic methods when testing glucose in urine during therapy with benzylpenicillin. False positive results can occur with the use of non-enzymatic methods.
Benzylpenicillin may interfere with other diagnostic tests such as the Coombs test, tests for the determination of proteins in plasma and urine and the test for the determination of plasmatic uric acid (copper-chelate method).
Due to the lidocaine content (present in the ampoule), Lentocilin S should be used with caution in the following situations:
- presence of cardiovascular, hepatic or renal dysfunction, inflammation and/or infection at the injection site or sensitivity to local anesthetics of the amide type,
- children, the elderly and patients with acute illnesses or debilitated,
- patients on concomitant CNS depressant drugs.

ADVERSE REACTIONS

The most common undesirable effects of benzylpenicillin are hypersensitivity reactions, especially skin rashes. Anaphylactic reactions occurred occasionally, which have sometimes been fatal. The overall incidence of allergic reactions to penicillin ranges between 1 and 10%. Anaphylactic reactions occur in approximately 0.05% of patients, usually after parenteral administration.
The following undesirable effects were observed with benzylpenicillin:
Blood and lymphatic system disorders - Eosinophilia and hemolytic anemia (both with immunological basis), leukopenia and thrombocytopenia. These effects are usually reversible after discontinuation of treatment.
Immune system disorders - Hypersensitivity reactions to penicillin cause a wide variety of clinical syndromes. Immediate reactions include anaphylaxis, laryngeal edema, angioedema, urticaria and maculopapular rashes. Late reactions include hemolytic anemia and immune complex self-limited sickness-like reactions, characterized by fever, malaise, urticaria, arthralgia, myalgia, lymphadenopathy and splenomegaly. In order to determine which patients will probably develop severe allergic reactions, hypersensitivity skin tests may be used. Jarisch – Herxheimer reaction.
Nervous system disorders - Benzylpenicillin is very irritating to the central and peripheral nervous systems. Neurotoxic reactions include anxiety, asthenia, cerebrovascular accident (CVA), confusion, dizziness, euphoria, nervousness, hallucinations, headache, neuropathy, neurovascular injury, localized or generalized seizures, coma, tremor and vasospasm at the administration site, and occur after parenteral administration of benzylpenicillin potassium. These reactions are most common when the benzylpenicillin is given daily in doses of more than 20,000,000 IU intravenously to renal impaired patients.
The accidental injection of preparations of benzylpenicillin into or near by the nerves may produce neuromuscular damage, which rarely may be permanent.
Rarely, inadvertent intravascular administration of benzathine benzylpenicillin or procaine benzylpenicillin, including direct administration into an artery - or adjacent to an artery - causes occlusion, thrombosis and severe neurovascular injury, especially in children.
Deep injection in the glutes gluteal muscles can cause paralysis, dysfunction and painful irritation of the sciatic nerve.
Repeated intramuscular injection of benzylpenicillin preparations in the anterolateral side of the thigh of newborns has rarely caused generalized muscular contractions, as well as atrophy and fibrosis of the quadriceps femoris muscle.
After intramuscular administration of benzathine benzylpenicillin may occurs Hoigné syndrome may occur, characterized by agitation accompanied by symptoms such as fear of impending death and visual and auditory hallucinations. Transversal myelitis with permanent paralysis, gangrene requiring amputation of fingers and the more proximal regions of the extremities, and necrosis with formation of scars surrounding the site of injection, have occurred after injections in the buttocks, thighs and deltoid muscle.
Eye disorders - Blurred vision, transient blindness.
Cardiac disorders - Hypotension, palpitations, syncope, tachycardia, vasodilation and vasovagal syndrome characterized by anxiety, sweating, hypotension, peripheral arterial vasodilation and bradycardia.
Cardiopulmonary arrest and death due to inadvertent IV administration.
Respiratory, thoracic and mediastinal disorders - Apnea, dyspnea, hypoxia, pulmonary embolism and pulmonary hypertension.
Gastro-intestinal disorders - Intestinal necrosis, melena, nausea, vomiting, and pseudomembranous colitis, which can arise during or after treatment.
Hepatobiliary disorders - Transient increases in SGOT, hepatitis and cholestatic jaundice.
Skin and subcutaneous tissue disorders - Diaphoresis, pruritus and urticaria.
Musculo-skeletal, connective tissue and bone disorders - Arthritis, arthropathy, myoglobinuria, periostitis and rhabdomyolysis.
Renal and urinary disorders - Hematuria, neurogenic bladder, renal impairment, proteinuria and increased serum BUN and creatinine.
Reproductive system and breast disorders - Impotence and priapism
General disorders and administration site conditions - Parenteral administration of benzylpenicillin preparations may cause dose-related injection site reactions dose-related and are the result of a direct toxic effect of the drug. IM administration of high doses of benzylpenicillin benzathine (in particular more than 600,000 IU of benzylpenicillin) in a single injection site can result in painful tumefaction and endothelial injury on site. IM administration of benzylpenicillin has been associated with the occurrence of the following side effects at the administration site: inflammation, pain, abscess, edema, hemorrhage, cellulitis, atrophy and cutaneous ulceration. It has also been reported cases of fever and fatigue associated with the use of benzylpenicillin.

DRUG INTERACTIONS

Bacteriostatic antibiotics: Bacteriostatic antibiotics, such as tetracycline, erythromycin and chloramphenicol, may antagonize the bactericidal effect of benzylpenicillin by interfering with active bacterial growth necessary to benzylpenicillin’s effect.
Oral contraceptives: The efficacy of oral contraceptives may be impaired in case of concomitant therapy with benzylpenicillin, which may result in an unwanted pregnancy.
Women taking oral contraceptives should be alerted to this situation and should be informed about the need to adopt alternative methods of contraception.
Methotrexate: Penicillins may reduce the renal excretion of methotrexate causing a potential increase in its toxicity.
Probenecid: Probenecid decreases the renal tubular secretion of benzylpenicillin. Its concomitant use with benzylpenicillin can prolong blood levels of benzylpenicillin. Probenecid may be used therapeutically for this purpose.

Temporary Importation of Lentocilin©, (Benzathine Benzylpenicillin Tetrahydrate) Powder and diluent for suspension for injection, 1,200,000 units with Foreign, non-U.S. Labeling to Address Supply Shortage

Dear Healthcare Provider,

To address the shortages of Bicillin® L-A (penicillin G benzathine injectable suspension) in the United States, Mark Cuban Cost Plus Drug Company, PBC (“MCCPDC”) is coordinating with the U.S. Food and Drug Administration (FDA) to temporarily import Lentocilin© (Benzathine Benzylpenicillin Tetrahydrate) Powder and diluent for suspension for injection, 1,200,000 units into the United States. Benzathine benzylpenicillin is another name for Penicillin G benzathine.

Lentocilin©, (Benzathine Benzylpenicillin Tetrahydrate) Powder and diluent for suspension for injection 1,200,000 units, manufactured and marketed in Portugal by Laboratórios Atral S.A., is not FDA-approved.

Effective immediately, MCCPDC will distribute the following presentations of Lentocilin©, (Benzathine Benzylpenicillin Tetrahydrate) Powder and diluent for suspension for injection 1,200,000 units to address the shortage:

Product Description - LENTOCILIN S 1200 1,200,000 units/4ML

Strength - 1,200,000 units/4 ml

Pack Size - 1 unit

NDC # - 84383-110

Batch # - V055V007497V

Expiration Date - 03/31/2028

The barcode on the imported product label may not register accurately on the U.S. scanning systems. Institutions should manually input the imported product information into their systems and confirm that the barcode, if scanned, provides correct information. Alternative procedures should be followed to assure that the correct drug product is being used and administered to individual patients.

In addition, the packaging of the imported product does include serialization information. Lab Atral does not meet the Drug Supply Chain Security Act (DSCSA) requirements for the Interoperable Exchange of Information for Tracing of Human, Finished Prescription Drugs. However, the company is not registered in the GS1 system in US, thus the tracking function is not available.

There are key differences between the FDA approved Bicillin® L-A and Lentocilin©

- Lentocilin© labeling does not have a boxed warning. Please refer to the Bicillin L-A boxed warning.
- Lentocilin© carton labeling does not have the warning “Fatal if given by other routes”. However, Lentocilin's product information states that "Lentocilin S Suspension for injection must be administered EXCLUSIVELY by DEEP INTRAMUSCULAR (IM) injection.”.
- Lentocilin© contains soy phospholipids and may cause hypersensitivity reactions (urticaria, anaphylactic shock) in patients with a history of allergy to soybeans.
- Lentocilin© is supplied as powder for reconstitution compared to prefilled disposable syringes for Bicillin L-A. Follow instructions for the preparation of an intramuscular injection of Lentocilin® in the Preparation section below.
- The volume of Lentocilin© 1,200,000 units after reconstitution is around 4 mL compared to 2 mL for Bicillin L-A 1,200,000 units.
- Lentocilin© labeling includes detailed instructions for deep intramuscular administration in the Warnings section below:

- Administer Lentocilin S suspension EXCLUSIVELY by DEEP INTRAMUSCULAR INJECTION in the external upper quadrant of the buttock.
- In children and infants, the IM injections should be done, preferably, in the middle of the external lateral side of the thigh.
- In infants younger than 2 years, and if considered necessary, the dosage may be divided and administered in two separate sites.
- The IM injection site should be changed in case of repeated doses.

- Lentocilin© should be stored below 25ºC, in the original package to protect from light and moisture. Following reconstitution, benzylpenicillin benzathine should be used immediately.
- Lentocilin© will be available only by prescription in the U.S. However, the imported product does not have the statement “Rx only” on the labeling. An equivalent expression is included in carton box (Medicinal product subject to medical prescription).

Reporting Adverse Events:

Healthcare providers should report adverse events associated with the use of Lab Atral’s Lentocilin© to MCCPDC by phone: 682-428-8081; email: dtc_quality@costplusdrugs.com.

Adverse reactions or quality problems experienced with the use of this product may be reported to the FDA’s MedWatch Adverse Event Reporting program either online, by regular mail or by fax:

- Complete and submit the report Online: www.fda.gov/medwatch/report.htm
- Regular Mail or Fax: Download form https://www.accessdata.fda.gov/scripts/medwatch/index.cfm or call 1-800-332-1088 to request a reporting form, then complete and return to the address on the pre-addressed form or submit by fax to 1-800-FDA-0178 (1-800-332-0178).

Please ensure that your staff and others in your institution who may be involved in the administration of Lab Atral’s Lentocilin© receive a copy of this letter and review the information.

To place an order, please contact TopRx at support@toprx.com or 1-800-542-8677.

This letter is not intended as a complete description of the benefits and risks related to the use of Lab Atral’s Lentocilin©. Please refer to the enclosed full prescribing information.

For additional information, please contact Mark Cuban Cost Plus Drug Company, PBC. at 682-428-8081; email: dtc_quality@costplusdrugs.com.